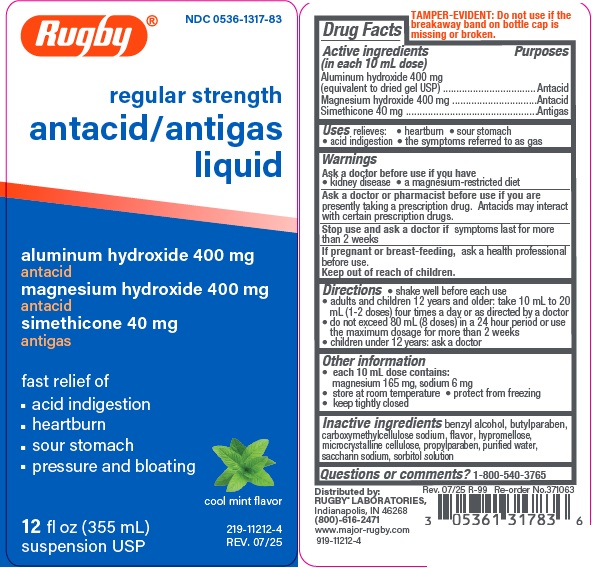 DRUG LABEL: REGULAR STRENGTH ANTACID/ANTIGAS
NDC: 0536-1317 | Form: SUSPENSION
Manufacturer: RUGBY LABORATORIES
Category: otc | Type: HUMAN OTC DRUG LABEL
Date: 20251117

ACTIVE INGREDIENTS: ALUMINUM HYDROXIDE 400 mg/10 mL; MAGNESIUM HYDROXIDE 400 mg/10 mL; DIMETHICONE 40 mg/10 mL
INACTIVE INGREDIENTS: BENZYL ALCOHOL; BUTYLPARABEN; CARBOXYMETHYLCELLULOSE SODIUM; HYPROMELLOSES; CELLULOSE, MICROCRYSTALLINE; PROPYLPARABEN; WATER; SACCHARIN SODIUM; SORBITOL SOLUTION

rug mlx mnt

Active ingredients (in each 10 mL dose)

Aluminum hydroxide 400 mg (equivalent to dried gel, USP)

Magnesium hydroxide 400 mg

Simethicone 40mg

Purposes

Antacid

Antigas

Uses

relieves

- heartburn
- sour stomach
- acid indigestion
- the symptoms referred to as gas

Warnings

Ask a doctor before use if you have

- kidney disease
- a magnesium-restricted diet

Ask a doctor or pharmacist before use if you are presently taking a prescription drug.

Antacids may interact with certain prescription drugs.

Stop use and ask a doctor if symptoms last more than 2 weeks

If pregnant or breast-feeding, ask a health professional before use.

Keep out of reach of children.

Directions

• shake well before each use

• adults and children 12 years and older: take 10 mL to 20 mL
(1-2 doses) four times a day or as directed by a doctor
• do not exceed 80 mL (8 doses) in a 24 hour period or use the
maximum dosage for more than 2 weeks
• children under 12 years: ask a doctor

Other information

• each 10 mL dose contains: magnesium 165 mg, sodium 6 mg
• store at room temperature

• protect from freezing
• keep tightly closed

Inactive ingredients

benzyl alcohol, butylparaben, carboxymethylcellulose sodium, flavor, hypromellose, microcrystalline cellulose, propylparaben, purified water, saccharin sodium, sorbitol solution

Questions or comments?

1-800-540-3765